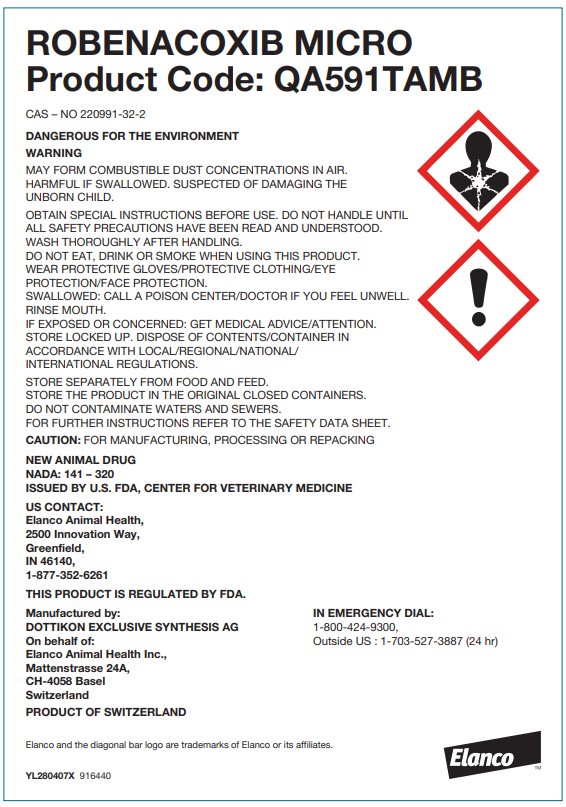 DRUG LABEL: ROBENACOXIB
NDC: 58198-5911 | Form: POWDER
Manufacturer: Elanco US Inc.
Category: other | Type: BULK INGREDIENT - ANIMAL DRUG
Date: 20251211

ACTIVE INGREDIENTS: ROBENACOXIB 25 kg/25 kg

Robenacoxib